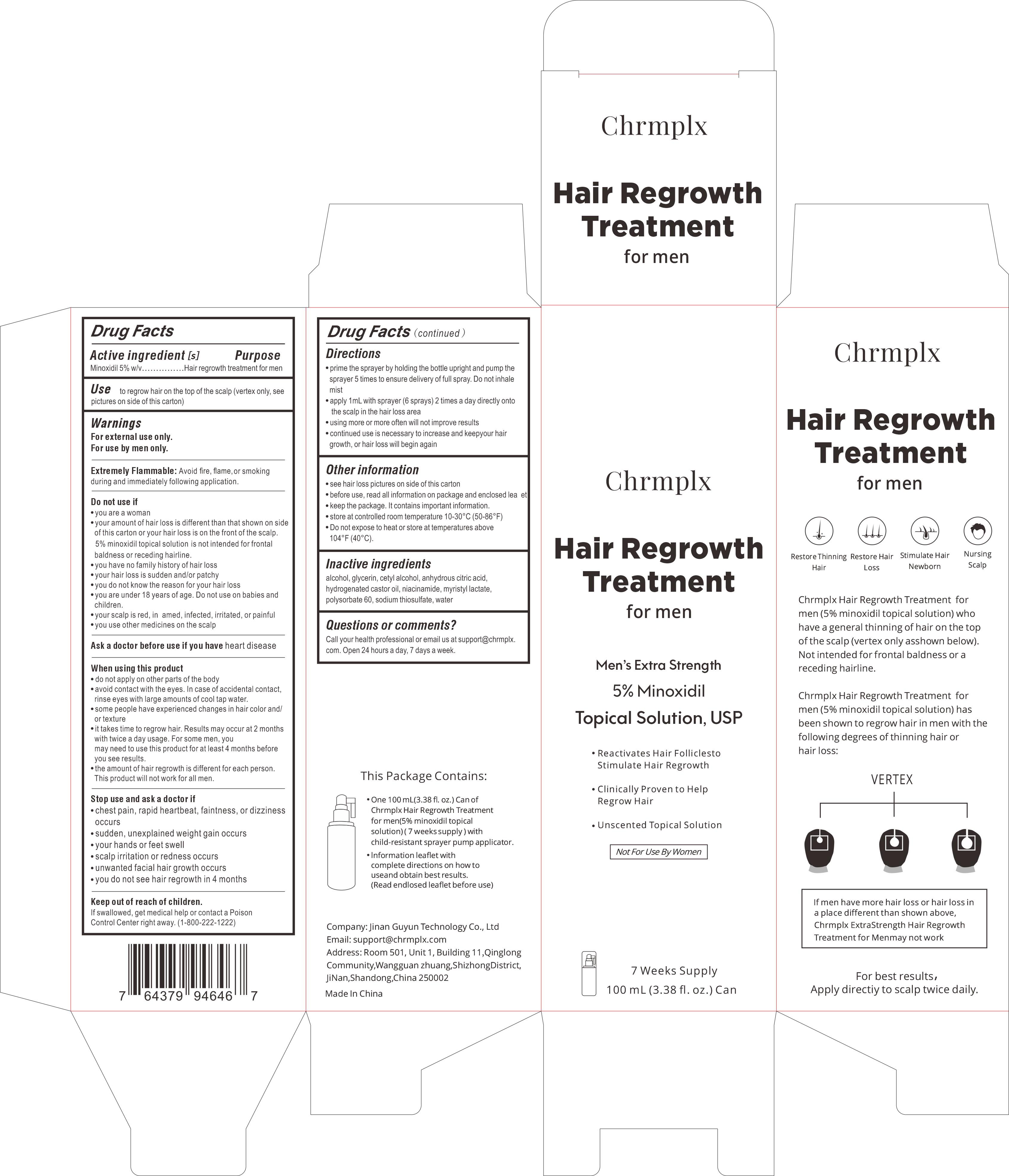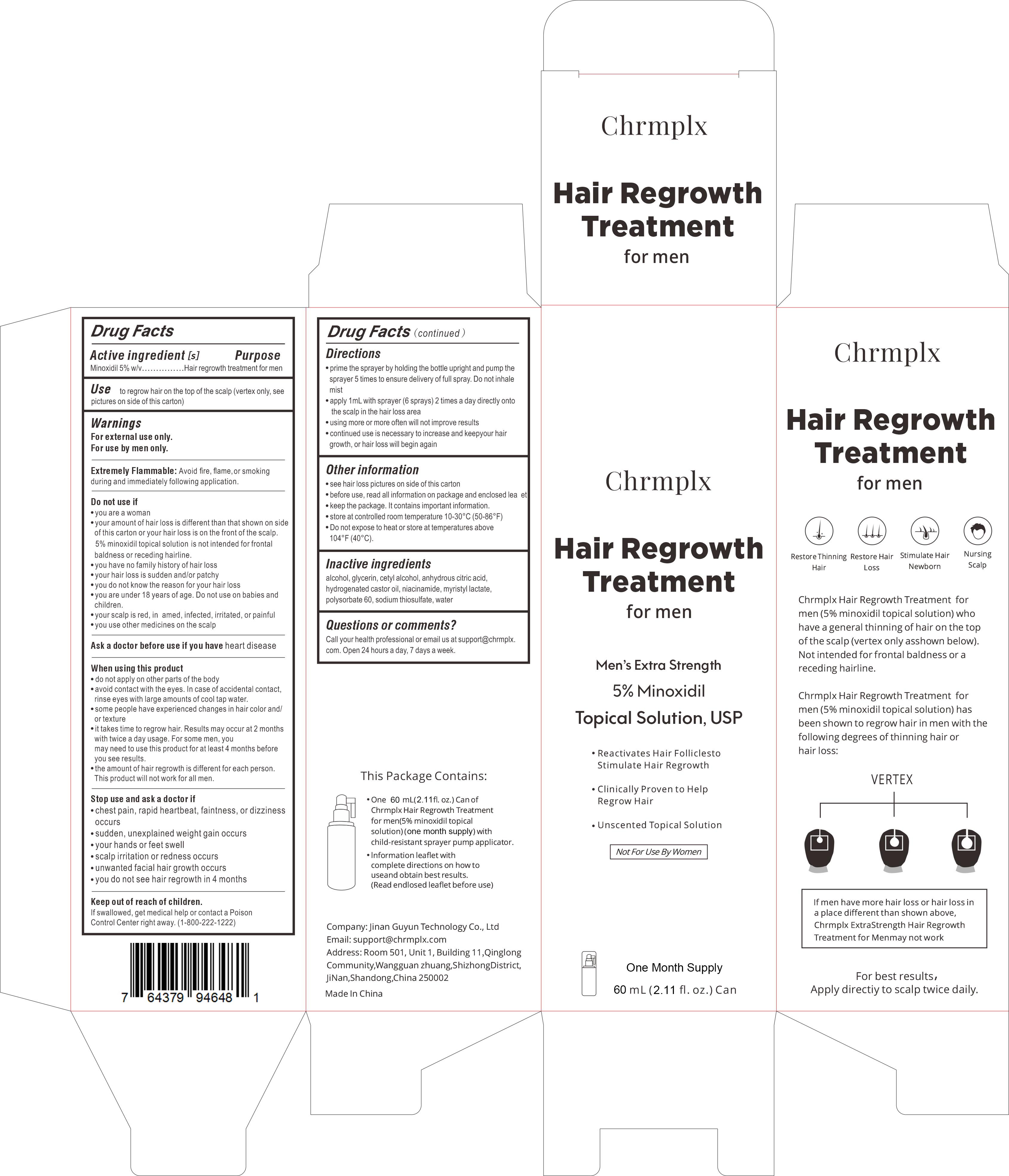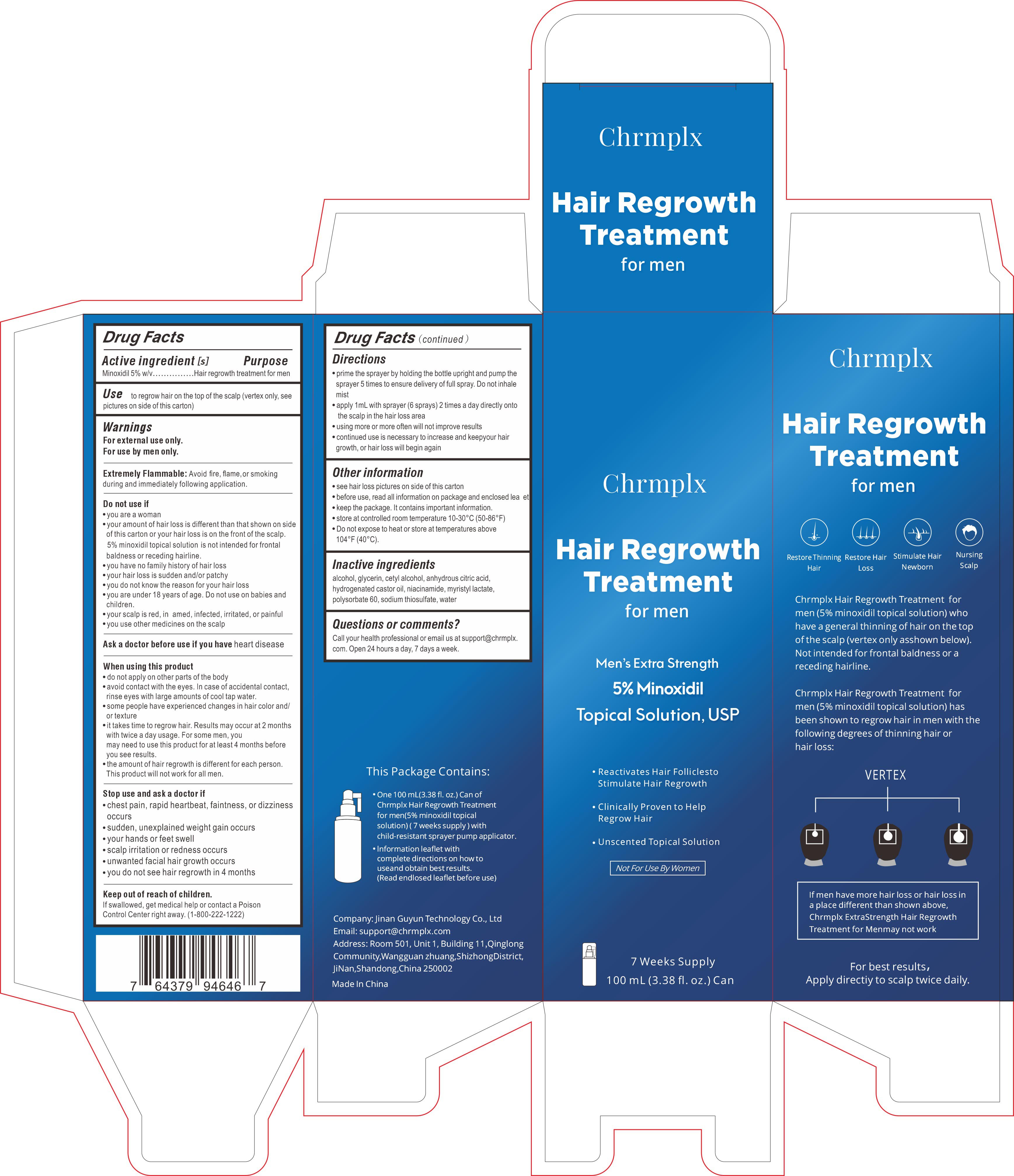 DRUG LABEL: Chrmplx Hair Regrowth Treatment
NDC: 83988-001 | Form: LIQUID
Manufacturer: Jinan Guyun Technology Co., Ltd
Category: otc | Type: HUMAN OTC DRUG LABEL
Date: 20240423

ACTIVE INGREDIENTS: MINOXIDIL 5 g/100 mL
INACTIVE INGREDIENTS: POLYSORBATE 60; WATER; NIACINAMIDE; MYRISTYL LACTATE; ALCOHOL; ANHYDROUS CITRIC ACID; CETYL ALCOHOL; HYDROGENATED CASTOR OIL; SODIUM THIOSULFATE; GLYCERIN

Chrmplx Hair Regrowth Treatment

Chrmplx Hair Regrowth Treatment

ACTIVE INGREDIENT

Minoxidil 5%

PURPOSE

Hair regrowth treatment for men

INDICATIONS AND USAGE

Use to regrow hair on the top of the scalp (vertex only, see pictures on side of this carton)

WARNINGS

For externaluse only.
For use by men only.

DO NOT USE

you are a woman.
your amount of hair loss is different than that shown on side of this carton or your hair loss is on the front of the scalp. 5% minoxidil topical solution is not intended for frontal baldness or receding hairline.
you have no family history of hair loss.
your hair loss is sudden and/or patchy.
you do not know the reason for your hair loss.
you are under 18 years of age. Do not use on babies and children.
your scalp is red, in amed, infected, irritated, or painful.
you use other medicines on the scalp

WHEN USING

do not apply on other parts of the body
avoid contact with the eyes.ln case of accidental contact, rinse eyes with large amounts of cooltap water.
some people have experienced changes in hair color and/ or texture
it takes time to regrow hair. Results may occur at 2 months with twice a day usage. For some men, you may need to use this product for atleast 4 months before you see results.
the amount of hair regrowth is different for each person.
This product will not work for all men.

STOP USE

chest pain,rapid heartbeat, faintness, or dizziness occurs
sudden,unexplained weight gain occurs
your hands or feet swell
scalp irritation or redness occurs
unwanted facialhair growth occurs
you do not see hair regrowth in 4 months

Keep out of reach of children.

lf swallowed, get medical help or contact a Poison

ControlCenterrightaway.(1-800-222-1222)

DOSAGE AND ADMINISTRATION

prime the sprayer by holding the bottle upright and pump the sprayer 5 times to ensure delivery of full spray. Do not inhale mist
apply 1mL with sprayer (6 sprays) 2 times a day directly onto the scalp in the hair loss area
using more or more often will not improve results
continued use is necessary to increase and keepyour hair growth, or hair loss will begin again

STORAGE AND HANDLING

store at controlled room temperature 10-30°C(50-86°F)
Do not expose to heat or store at temperatures above 104°F(40°C).

INACTIVE INGREDIENT

Alcohol
Glycerin
Cetyl alcohol
Anhydrous citric acid
Hydrogenated castor oil
Niacinamide
Myristyl lactate
Polysorbate 60
Sodium thiosulfate
Water